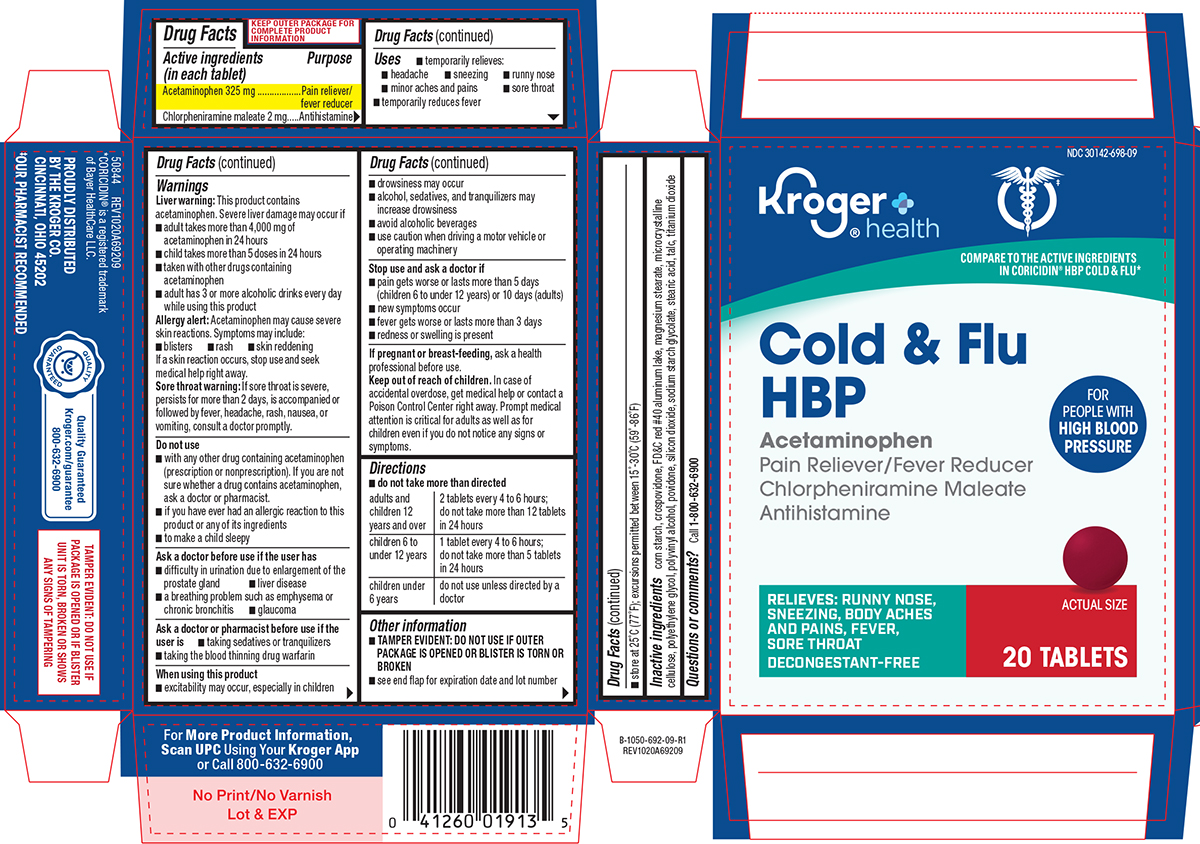 DRUG LABEL: Cold and Flu HBP
NDC: 30142-698 | Form: TABLET, FILM COATED
Manufacturer: Kroger Company
Category: otc | Type: HUMAN OTC DRUG LABEL
Date: 20260107

ACTIVE INGREDIENTS: ACETAMINOPHEN 325 mg/1 1; CHLORPHENIRAMINE MALEATE 2 mg/1 1
INACTIVE INGREDIENTS: STARCH, CORN; CROSPOVIDONE, UNSPECIFIED; FD&C RED NO. 40 ALUMINUM LAKE; MAGNESIUM STEARATE; MICROCRYSTALLINE CELLULOSE; POLYETHYLENE GLYCOL, UNSPECIFIED; POLYVINYL ALCOHOL, UNSPECIFIED; POVIDONE, UNSPECIFIED; SILICON DIOXIDE; SODIUM STARCH GLYCOLATE TYPE A POTATO; STEARIC ACID; TALC; TITANIUM DIOXIDE

Kroger 44-692

Active ingredients (in each tablet)

Acetaminophen 325 mg
Chlorpheniramine maleate 2 mg

Purpose

Pain reliever/fever reducer
Antihistamine

Uses

- temporarily relieves:
  - headache
  - sneezing
  - runny nose
  - minor aches and pains
  - sore throat
- temporarily reduces fever

Warnings

Liver warning: This product contains acetaminophen. Severe liver damage may occur if

- adult takes more than 4,000 mg of acetaminophen in 24 hours
- child takes more than 5 doses in 24 hours
- taken with other drugs containing acetaminophen
- adult has 3 or more alcoholic drinks every day while using this product

Allergy alert: Acetaminophen may cause severe skin reactions. Symptoms may include:

- blisters
- rash
- skin reddening

If a skin reaction occurs, stop use and seek medical help right away.

Sore throat warning: If sore throat is severe, persists for more than 2 days, is accompanied or followed by fever, headache, rash, nausea, or vomiting, consult a doctor promptly.

Do not use

- with any other drug containing acetaminophen (prescription or nonprescription). If you are not sure whether a drug contains acetaminophen, ask a doctor or pharmacist.
- if you have ever had an allergic reaction to this product or any of its ingredients
- to make a child sleepy

Ask a doctor before use if the user has

- difficulty in urination due to enlargement of the prostate gland
- liver disease
- glaucoma
- a breathing problem such as emphysema or chronic bronchitis

Ask a doctor or pharmacist before use if the user is

- taking sedatives or tranquilizers
- taking the blood thinning drug warfarin

When using this product

- excitability may occur, especially in children
- drowsiness may occur
- alcohol, sedatives, and tranquilizers may increase drowsiness
- avoid alcoholic beverages
- use caution when driving a motor vehicle or operating machinery

Stop use and ask a doctor if

- pain gets worse or lasts more than 5 days (children 6 to under 12 years) or 10 days (adults)
- new symptoms occur
- fever gets worse or lasts more than 3 days
- redness or swelling is present

If pregnant or breast-feeding,

ask a health professional before use.

Keep out of reach of children.

In case of accidental overdose, get medical help or contact a Poison Control Center right away. Prompt medical attention is critical for adults as well as for children even if you do not notice any signs or symptoms.

Directions

- do not take more than directed

adults and children 12 years and over | 2 tablets every 4 to 6 hours; do not take more than 12 tablets in 24 hours
children 6 to under 12 years | 1 tablet every 4 to 6 hours; do not take more than 5 tablets in 24 hours
children under 6 years | do not use unless directed by a doctor

Other information

- TAMPER EVIDENT: DO NOT USE IF OUTER PACKAGE IS OPENED OR BLISTER IS TORN OR BROKEN
- store at 25°C (77°F); excursions permitted between 15°-30°C (59°-86°F)
- see end flap for expiration date and lot number

Inactive ingredients

corn starch, crospovidone, FD&C red #40 aluminum lake, magnesium stearate, microcrystalline cellulose, polyethylene glycol, polyvinyl alcohol, povidone, silicon dioxide, sodium starch glycolate, stearic acid, talc, titanium dioxide

Questions or comments?

Call 1-800-632-6900

Principal display panel

NDC 30142-698-09

Kroger®
health

COMPARE TO THE ACTIVE INGREDIENTS
IN CORICIDIN® HBP COLD & FLU*

Cold & Flu
HBP
FOR
PEOPLE WITH
HIGH BLOOD
PRESSURE

Acetaminophen
Pain Reliever/Fever Reducer
Chlorpheniramine Maleate
Antihistamine

RELIEVES: RUNNY NOSE,
SNEEZING, BODY ACHES
AND PAINS, FEVER,
SORE THROAT
DECONGESTANT-FREE

ACTUAL
SIZE

20 TABLETS

PROUDLY DISTRIBUTED
BY THE KROGER CO.
CINCINNATI, OHIO 45202
‡OUR PHARMACIST RECOMMENDED

For More Product Information,
Scan UPC Using Your Kroger App
or Call 800-632-6900

Quality Guaranteed
Kroger.com/guarantee
800-632-6900

50844 REV1020A69209
*CORICIDIN® is a registered trademark
of Bayer HealthCare LLC.

TAMPER EVIDENT: DO NOT USE IF
PACKAGE IS OPENED OR IF BLISTER
UNIT IS TORN, BROKEN OR SHOWS
ANY SIGNS OF TAMPERING

Kroger 44-692